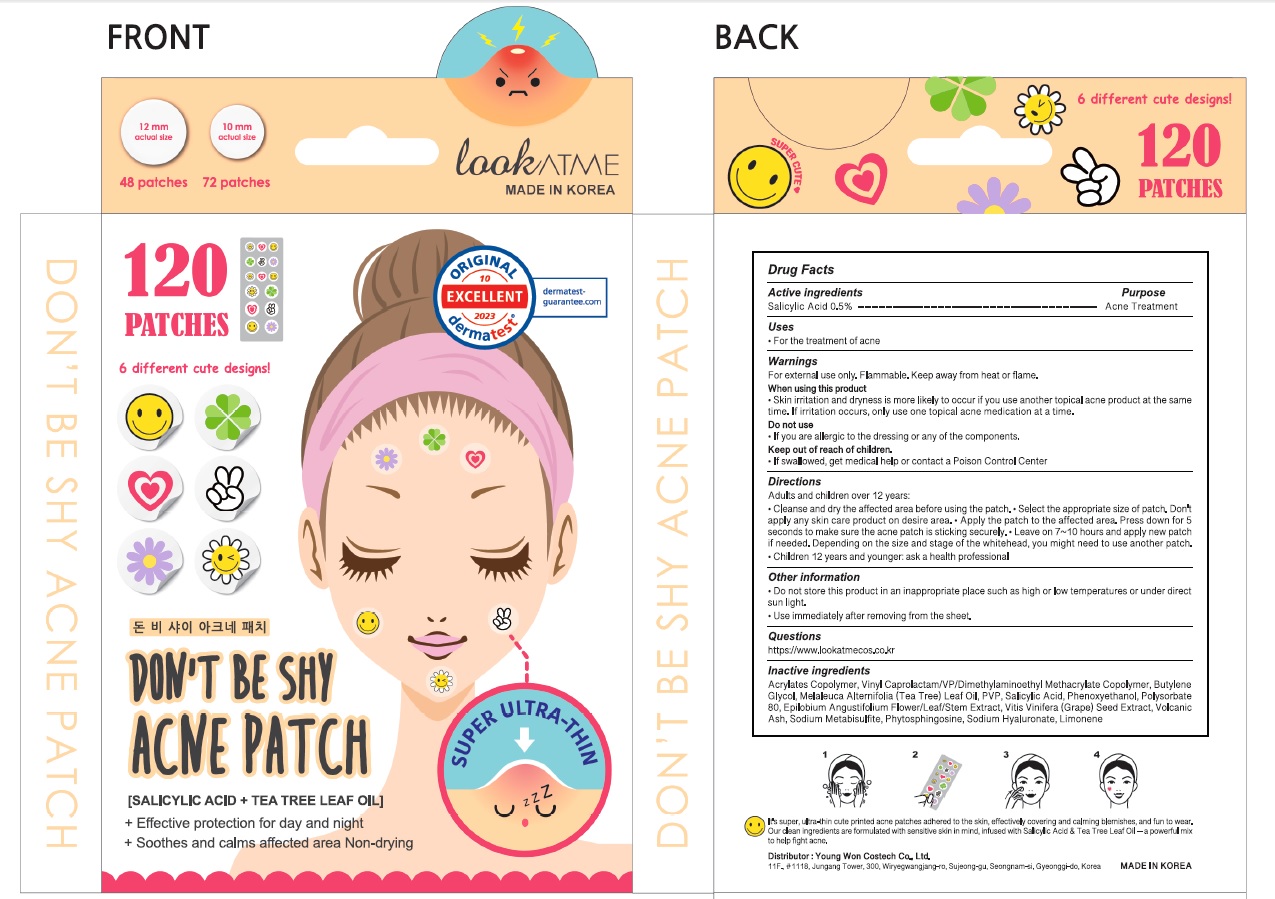 DRUG LABEL: DONT BE SHY ACNE
NDC: 72169-540 | Form: PATCH
Manufacturer: Youngwon Costech Co.,ltd.
Category: otc | Type: HUMAN OTC DRUG LABEL
Date: 20240216

ACTIVE INGREDIENTS: Salicylic Acid 0.005 g/1 1
INACTIVE INGREDIENTS: Butylene Glycol; TEA TREE OIL; Phenoxyethanol

ACTIVE INGREDIENT

Salicylic Acid 0.5%

INACTIVE INGREDIENTS

Acrylates Copolymer, Vinyl Caprolactam/VP/Dimethylaminoethyl Methacrylate Copolymer, Butylene Glycol, Melaleuca Alternifolia (Tea Tree) Leaf Oil, PVP, Salicylic Acid, Phenoxyethanol, Polysorbate 80, Epilobium Angustifolium Flower/Leaf/Stem Extract, Vitis Vinifera (Grape) Seed Extract, Volcanic Ash, Sodium Metabisulfite, Phytosphingosine, Sodium Hyaluronate, Limonene

PURPOSE

Acne Treatment

WARNINGS

For external use only. Flammable. Keep away from heat or flame.

When using this product
• Skin irritation and dryness is more likely to occur if you use another topical acne product at the same time. If irritation occurs, only use one topical acne medication at a time.

Do not use
• If you are allergic to the dressing or any of the components.

Keep out of reach of children
• If swallowed, get medical help or contact a Poison Control Center

KEEP OUT OF REACH OF CHILDREN

If swallowed, get medical help or contact a Poison Control Center

Uses

■ For the treatment of acne

Directions

Adults and children over 12 years:
• Cleanse and dry the affected area before using the patch. • Select the appropriate size of patch. Don't apply any skin care product on desire area. • Apply the patch to the affected area. Press down for 5 seconds to make sure the acne patch is sticking securely. • Leave on 7~10 hours and apply new patch if needed. Depending on the size and stage of the whitehead, you might need to use another patch.
• Children 12 years and younger: ask a health professional

Other Information

■ Do not store this product in an inappropriate place such as high or low temperatures or under direct sun light.
■ Use immediately after removing from the sheet.

QUESTIONS

https://www.lookatmecos.co.kr